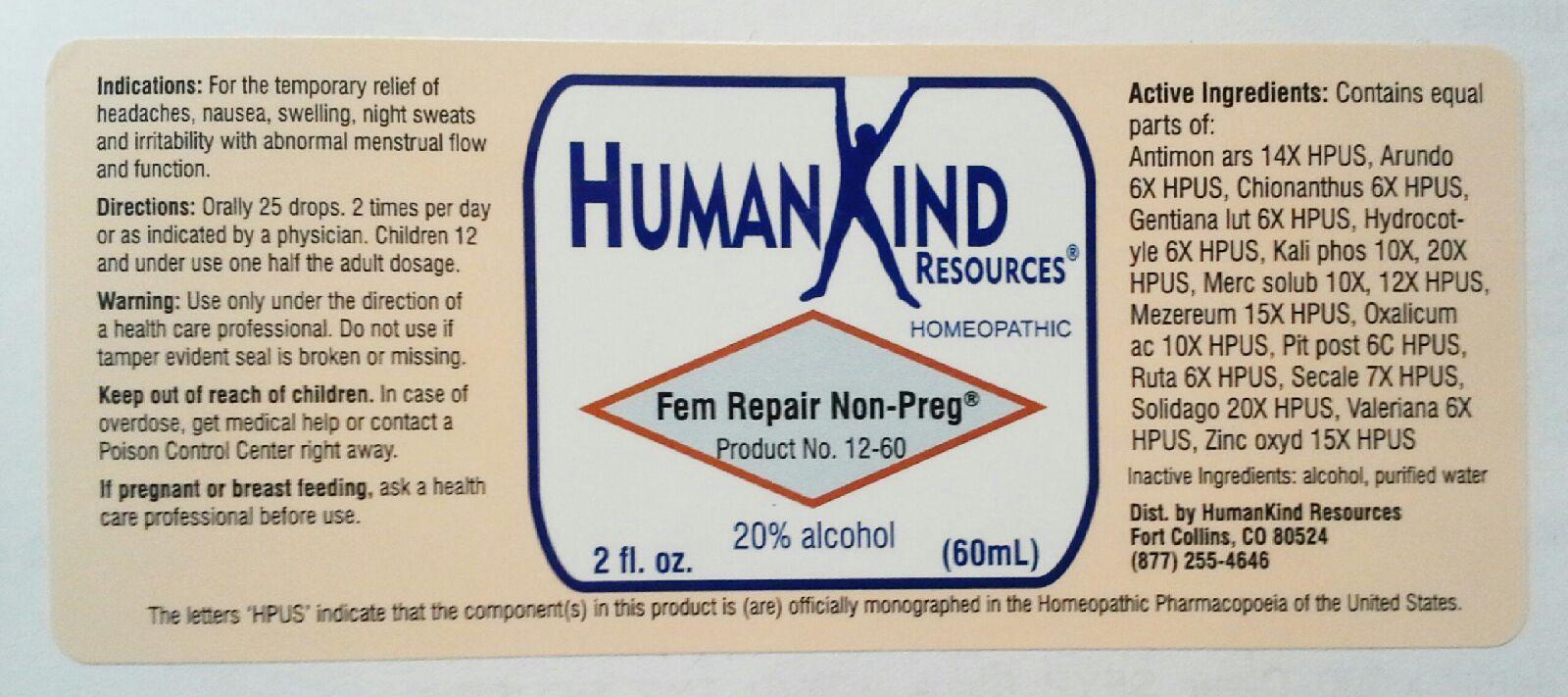 DRUG LABEL: Fem Repair Non-Preg
NDC: 64616-090 | Form: LIQUID
Manufacturer: Vitality Works, Inc.
Category: homeopathic | Type: HUMAN PRESCRIPTION DRUG LABEL
Date: 20251217

ACTIVE INGREDIENTS: ANTIMONY ARSENATE 14 [hp_X]/1 mL; CHRYSOPOGON ZIZANIOIDES ROOT 6 [hp_X]/1 mL; CHIONANTHUS VIRGINICUS BARK 6 [hp_X]/1 mL; GENTIANA LUTEA ROOT 6 [hp_X]/1 mL; CENTELLA ASIATICA 6 [hp_X]/1 mL; POTASSIUM PHOSPHATE, DIBASIC 20 [hp_X]/1 mL; MERCURIUS SOLUBILIS 12 [hp_X]/1 mL; DAPHNE MEZEREUM BARK 15 [hp_X]/1 mL; OXALIC ACID DIHYDRATE 10 [hp_X]/1 mL; SUS SCROFA PITUITARY GLAND 6 [hp_C]/1 mL; RUTA GRAVEOLENS FLOWERING TOP 6 [hp_X]/1 mL; CLAVICEPS PURPUREA SCLEROTIUM 7 [hp_X]/1 mL; SOLIDAGO VIRGAUREA FLOWERING TOP 20 [hp_X]/1 mL; VALERIANA OFFICINALIS WHOLE 6 [hp_X]/1 mL; ZINC OXIDE 15 [hp_X]/1 mL
INACTIVE INGREDIENTS: ALCOHOL; WATER

Fem Repair Non-Preg

Fem Repair Non-Preg

Antimonium Arsenicum 14x Kali Phosphoricum 10X, 20X Ruta Graveolens 6X

Arundo Mauritanica 6X Mercurius Solubilis 10X, 12X Secale Cornutum 7X

Chionanthus Virginica 6X Mezereum 15X Solidago Vigaurea 18X

Gentiana Lutea 6X Oxalicum Acidum 10X Valeriana Officinalis 4X

Hydrocotyle Asiatica 6X Pituitarum Posterior 6C Zinc Oxydatum 13X

Fem Repair Non-Preg

Alcohol, Purified Water

Fem Repair Non-Preg

Use only under the direction of a health care professional. Do not use if tamper evident seal is broken of missing.

Fem Repair Non-Preg

Keep out of reach of children. In case of overdose, get medical help or contact a Poison Control Center right away.

Fem Repair Non-Preg

For the temporary relief of headaches, nausea, swelling, night sweats and irritability with abnormal menstrual flow and function.

Fem Repair Non-Preg

Orally 25 drops, 2 times per day or as indicated by a physician. Children 12 and under use one half the adult dosage.

Fem Repair Non-Preg

Assist the body in repair of glandular and reproductive tissue, and re-establishes chemical and hormonal connections.